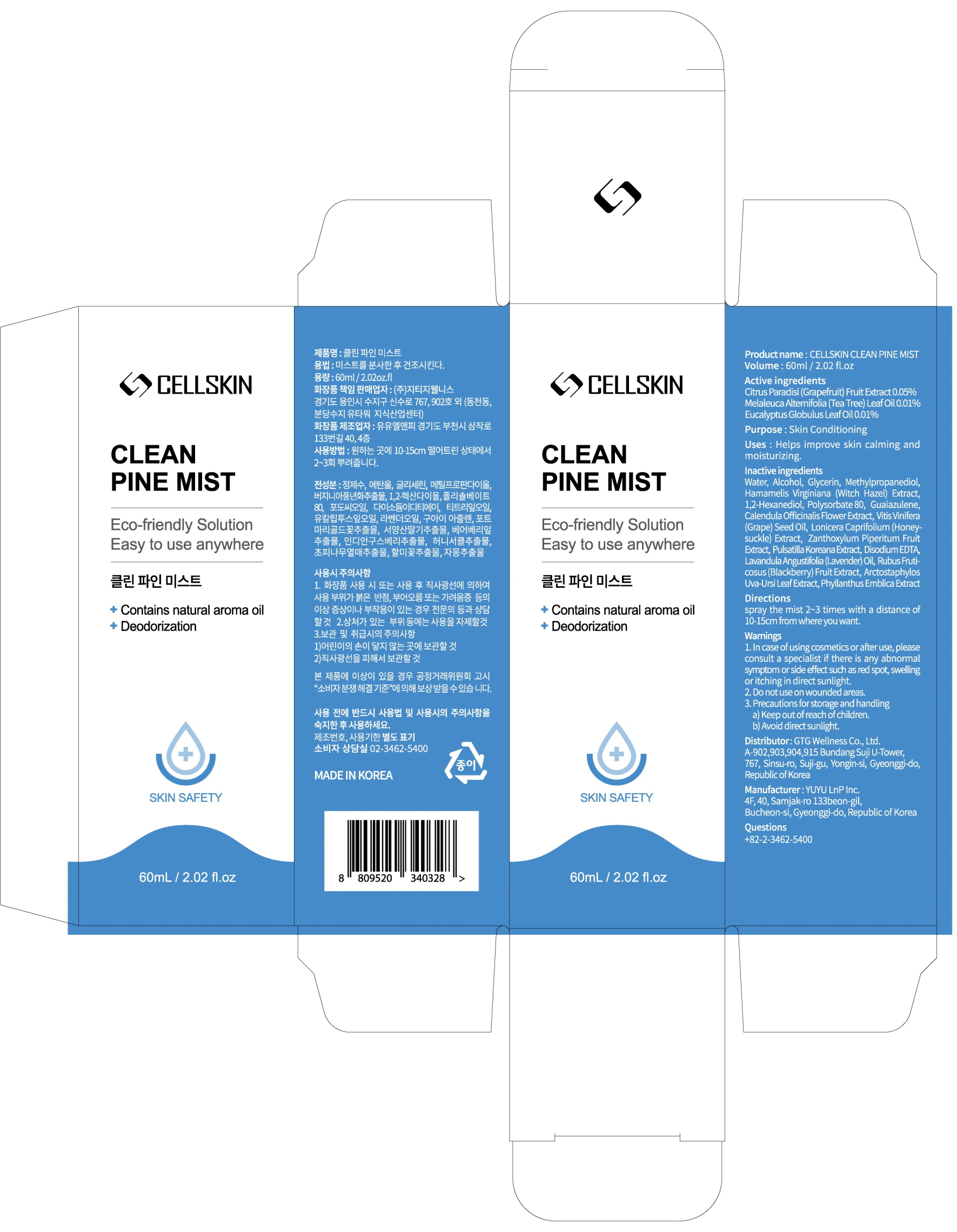 DRUG LABEL: CELLSKIN CLEAN PINE MIST
NDC: 71080-0019 | Form: SPRAY
Manufacturer: GTG Wellness Co., Ltd.
Category: otc | Type: HUMAN OTC DRUG LABEL
Date: 20200713

ACTIVE INGREDIENTS: GRAPEFRUIT 0.05 g/100 mL; TEA TREE OIL 0.01 g/100 mL; EUCALYPTUS OIL 0.01 g/100 mL
INACTIVE INGREDIENTS: Water; Alcohol; Glycerin; Methylpropanediol; Witch Hazel; 1,2-Hexanediol

ACTIVE INGREDIENTS

Citrus Paradisi (Grapefruit) Fruit Extract 0.05%
Melaleuca Alternifolia (Tea Tree) Leaf Oil 0.01%
Eucalyptus Globulus Leaf Oil 0.01%

INACTIVE INGREDIENTS

Water, Alcohol, Glycerin, Methylpropanediol, Hamamelis Virginiana (Witch Hazel) Extract, 1,2-Hexanediol, Polysorbate 80, Guaiazulene, Calendula Officinalis Flower Extract, Vitis Vinifera (Grape) Seed Oil, Lonicera Caprifolium (Honeysuckle) Extract, Zanthoxylum Piperitum Fruit Extract, Pulsatilla Koreana Extract, Disodium EDTA, Lavandula Angustifolia (Lavender) Oil, Rubus Fruticosus (Blackberry) Fruit Extract, Arctostaphylos Uva-Ursi Leaf Extract, Phyllanthus Emblica Extract

PURPOSE

Skin Conditioning

WARNINGS

1. In case of using cosmetics or after use, please consult a specialist if there is any abnormal symptom or side effect such as red spot, swelling or itching in direct sunlight.
2. Do not use on wounded areas.
3. Precautions for storage and handling
a) Keep out of reach of children.
b) Avoid direct sunlight.

KEEP OUT OF REACH OF CHILDREN

Uses

Helps improve skin calming and moisturizing.

Directions

Spray the mist 2~3 times with a distance of 10-15cm from where you want.

QUESTIONS

82-2-3462-5400